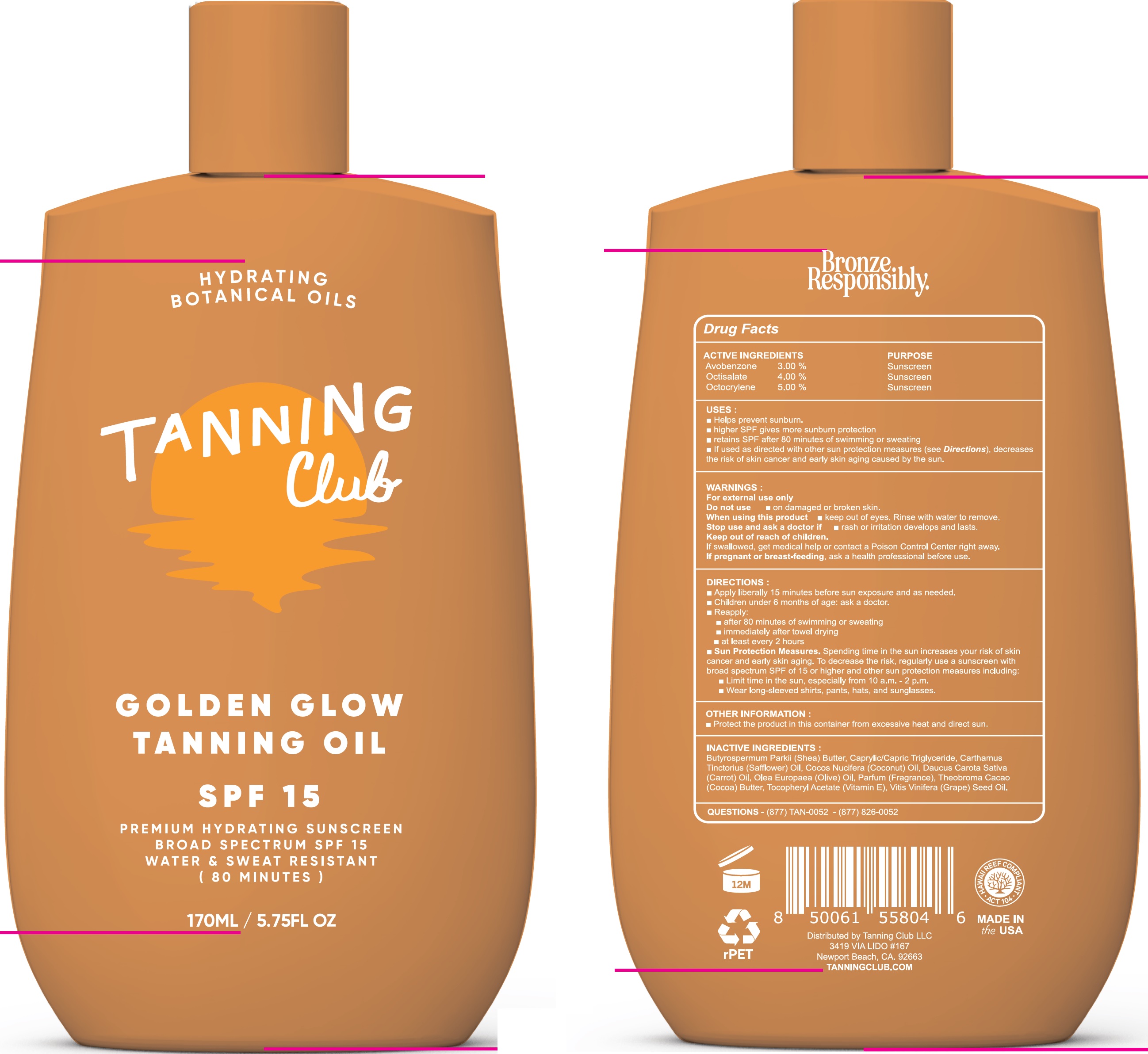 DRUG LABEL: Tanning Club Golden Glow Tanning Oil SPF 15
NDC: 84562-872 | Form: OIL
Manufacturer: TANNING CLUB, LLC
Category: otc | Type: HUMAN OTC DRUG LABEL
Date: 20250806

ACTIVE INGREDIENTS: AVOBENZONE 30 mg/1 mL; OCTISALATE 40 mg/1 mL; OCTOCRYLENE 50 mg/1 mL
INACTIVE INGREDIENTS: SHEA BUTTER; MEDIUM-CHAIN TRIGLYCERIDES; SAFFLOWER; COCONUT OIL; COCOA; .ALPHA.-TOCOPHEROL ACETATE; GRAPE SEED OIL

Tanning Club Golden Glow Tanning Oil SPF 15

ACTIVE INGREDIENTS

Avobenzone 3.00%
Octisalate 4.00%
Octocrylene 5.00%

PURPOSE

Sunscreen

USES:

- Helps prevent sunburn.
- higher SPF gives more sunburn protection
- retains SPF after 80 minutes of swimming or sweating
- If used as directed with other sun protection measures (see Directions), decreases the risk of skin cancer and early skin aging caused by the sun.

WARNINGS:

For external use only

Do not use

- on damaged or broken skin.

When using this product

- keep out of eyes. Rinse with water to remove.

Stop use and ask a doctor if

- rash or irritation develops and lasts.

Keep out of reach of children.

If swallowed, get medical help or contact a Poison Control Center right away.

If pregnant or breast-feeding,

ask a health professional before use.

DIRECTIONS:

- Apply liberally 15 minutes before sun exposure and as needed.
- Children under 6 months of age: ask a doctor.
- Reapply:
- after 80 minutes of swimming or sweating
- immediately after towel drying
- at least every 2 hours
- Sun Protection Measures.Spending time in the sun increases your risk of skin cancer and early skin aging. To decrease the risk, regularly use a sunscreen with broad spectrum SPF of 15 or higher and other sun protection measures including:
- Limit time in the sun, especially from 10 a.m.-2 p.m.
- Wear long-sleeved shirts, pants, hats, and sunglasses.

OTHER INFORMATION:

- Protect the product in this container from excessive heat and direct sun.

INACTIVE INGREDIENTS:

Butyrospermum Parkii (Shea) Butter, Caprylic/Capric Triglyceride, Carthamus Tinctorius (Safflower) Oil, Cocos Nucifera (Coconut) Oil, Parfum (Fragrance), Thebroma Cacao (Cocoa) Butter, Tocopheryl Acetate (Vitamin E), Vitis Vinefera (Grape) Seed Oil.

QUESTIONS

- (877) TAN-0052 - (877) 826-0052